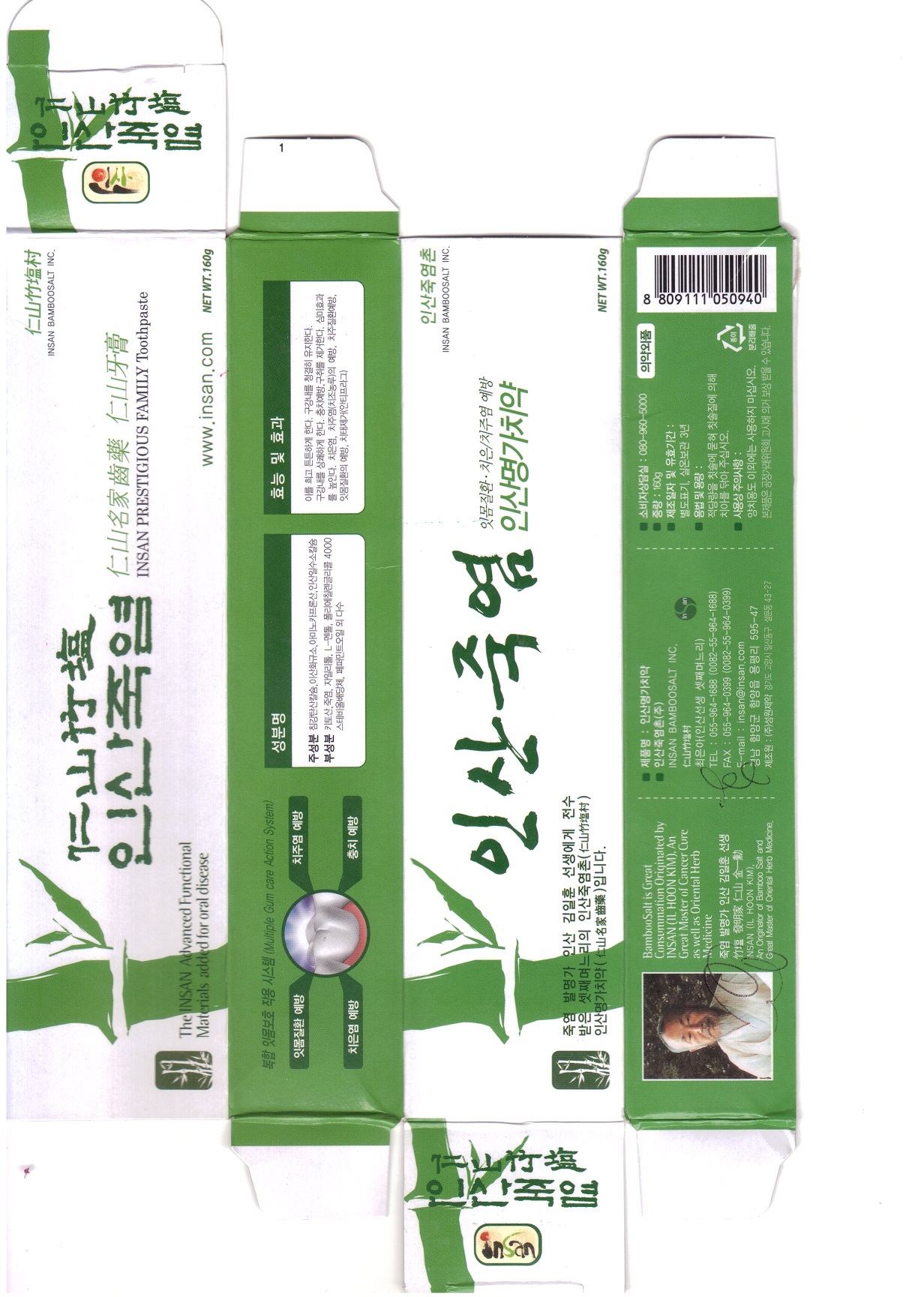 DRUG LABEL: Insan Bamboosalt toothpaste
NDC: 75958-1001 | Form: PASTE, DENTIFRICE
Manufacturer: Insan Bamboo Salt Inc
Category: otc | Type: HUMAN OTC DRUG LABEL
Date: 20110212

ACTIVE INGREDIENTS: CALCIUM CARBONATE 31.25 g/100 g
INACTIVE INGREDIENTS: SILICON DIOXIDE; ANHYDROUS DIBASIC CALCIUM PHOSPHATE; AMINOCAPROIC ACID; GLYCERIN; SORBITOL; CARBOXYMETHYLCELLULOSE SODIUM; SODIUM LAURYL SULFATE; POLYETHYLENE GLYCOL 4000; XYLITOL; LEVOMENTHOL; CHITOSAN OLIGOSACCHARIDE; SODIUM CHLORIDE; PEPPERMINT OIL; WATER

Drug Facts

active ingredient: precipitated calcium carbonate

inactive ingredient: silicon dioxide, dibasic calcium phosphate, aminocaproic acid, glycerine, D-sorbitol, sodium carboxymethylcellulose, sodium lauryl sulfate, polyethyleneglycol 4000, xylitol, L-menthol, chitosan, bamboo salt, steviol slycoside, peppermint oil, dionized water

PURPOSE

for dental care

keep out of reach of the children

DOSAGE AND ADMINISTRATION

brush your teeth by putting appropriate amount of tooth paste

do not use other than oral cavity

INDICATIONS AND USAGE

Make teeth strong. Clean and refresh oral cavity. Prevent dental cavities and bad breath.
Prevent from gingivitis, paradentitis, periodontal disease and gum disease and anti plaque.